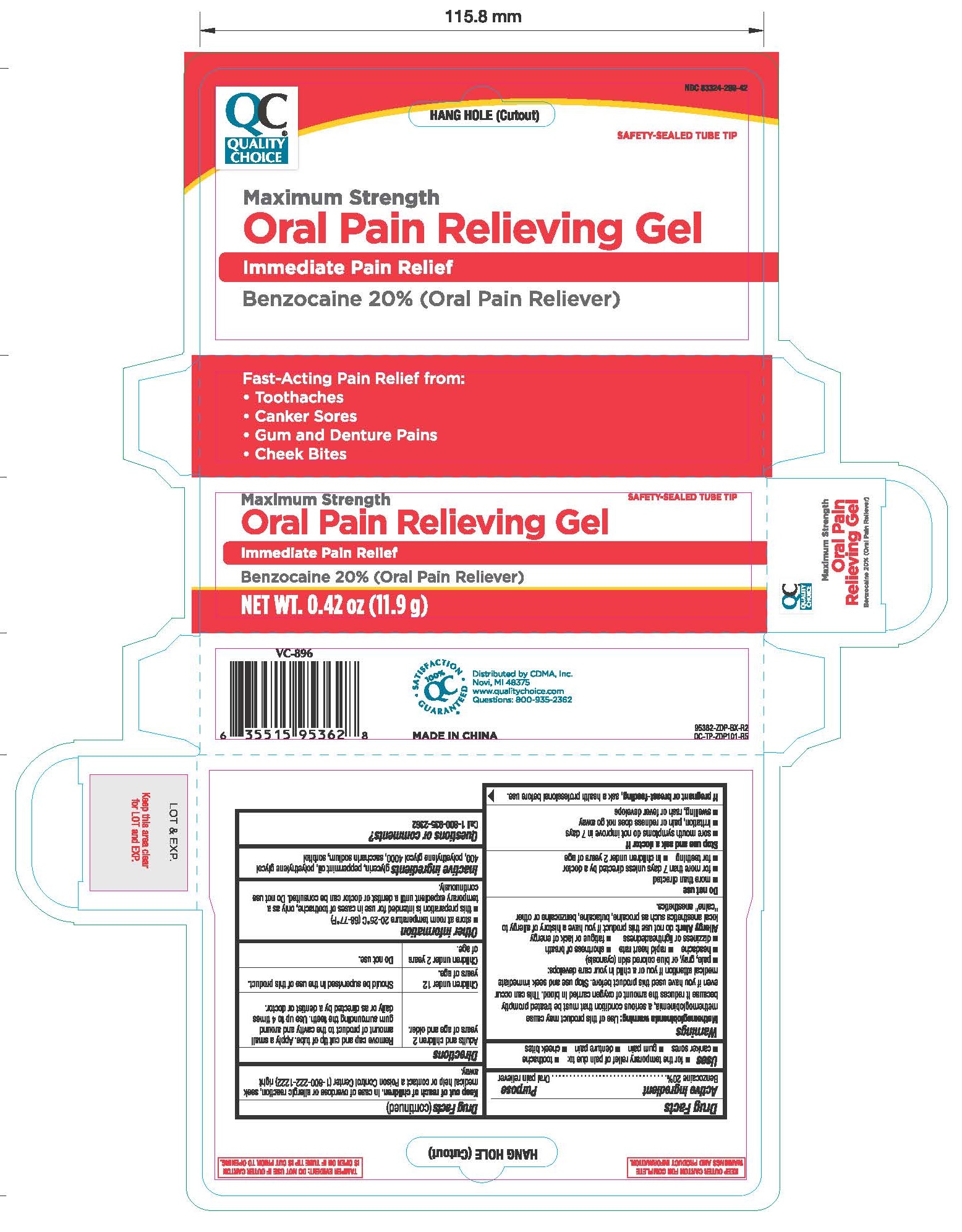 DRUG LABEL: Quality Choice
NDC: 83324-299 | Form: GEL
Manufacturer: Chain Drug Marketing Association, Inc.
Category: otc | Type: HUMAN OTC DRUG LABEL
Date: 20251016

ACTIVE INGREDIENTS: BENZOCAINE 200 mg/1 g
INACTIVE INGREDIENTS: PEPPERMINT OIL; POLYETHYLENE GLYCOL 4000; GLYCERIN; POLYETHYLENE GLYCOL 400; SACCHARIN SODIUM; SORBITOL

QC Maximum Strength Oral Analgesic 0.42oz 95362 (Benzocaine)

Active Ingredient Purpose

Benzocaine 20%................................Oral pain reliever

Uses

- for the temporary relief of pain due for:
- toothache
- canker sores
- gum pain
- denture pain
- cheek bites

Warnings

Methemoglobinemia warning: Use of this product may cause methemoglobinemia, a serious condition that must be treated promptly because it reduces the amount of oxygen carried blood. This can occur even I you have used this product before. Stop use and seek immediate medical attention if you are a child in your care develops:

- pale, gay, or blue colored skin (cyanosis)
- headache
- rapid heart rate
- shortness of breath
- dizziness or lightheartedness
- fatigue or lack of energy

Allergy Alert: do not use this product if you have a history of allergy to local anethetics as procaine, bucaine, benzocaine or other "caine" anesthetics.

Do not use

- more than directed
- for more than 7 days unless directed by a doctor
- for teething
- in children under 2 years of age

Stop use and ask a doctor if

- sore mouth symptoms do not improve in 7 days
- irritation, pain or redness does not go away
- swelling, rash or fever develops

PREGNANCY OR BREAST FEEDING

If pregnant or breast-feeding, ask a health professional before use.

Keep out of reach of children. In case of overdose or allergic reaction, seek medical help or contact a Poison Control Center (1-800-222-1222) right away.

Directions

Adults and children 2 years of age and older | Remove cap and cut tip of tube. Apply a small amount of product to the cavity and around gum surrounding the teeth. Use up to 4 times daily or as directed by a dentist or doctor.
Children under 12 years of age | Should be supervised in the use of this product
Children under 2 years of age | Do not use

Other information

- store at room temperature 20-25º (68-77ºF)
- this preparation is intended for use in cases of toothache, only as a temporary expedient until a dentist or doctor can be consulted. Do not use continuously.

Inactive ingredient glycerin, peppermint oil, polyethylene glycol 400, polyethylene glycol 4000, saccharin sodium, sorbitol

DOSAGE AND ADMINISTRATION

Distributed by CDMA, INC

Novi, MI 48375

Made in China